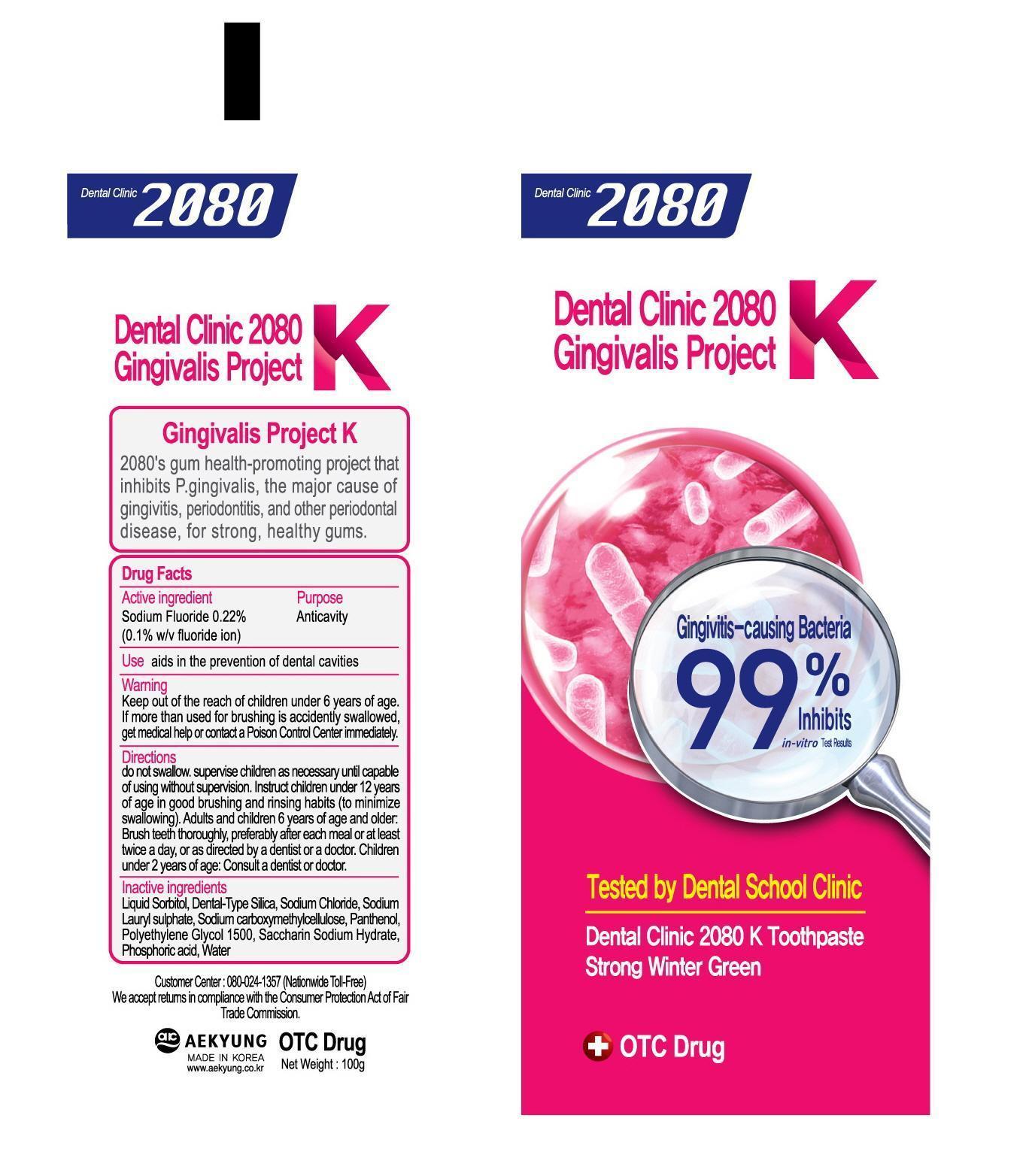 DRUG LABEL: Dental Clinic 2080 K Strong Winter Green
NDC: 67225-0002 | Form: PASTE, DENTIFRICE
Manufacturer: Aekyung Ind. Co., Ltd.
Category: otc | Type: HUMAN OTC DRUG LABEL
Date: 20140521

ACTIVE INGREDIENTS: SODIUM FLUORIDE 0.1 g/100 g
INACTIVE INGREDIENTS: POLYGLUCOSE SORBITOL CARBOXYMETHYL ETHER; SILICA DIMETHYL SILYLATE; SODIUM CHLORIDE; SODIUM LAURYL SULFATE; CARBOXYMETHYLCELLULOSE SODIUM; PANTHENOL; POLYETHYLENE GLYCOL 1500; SACCHARIN SODIUM; PHOSPHORIC ACID; WATER

Dental Clinic 2080 K Toothpaste Strong Winter Green

Active Ingredient

Sodium Fluoride 0.22% (0.1% w/v fluoride ion)

Purpose

Anticavity

Use

Aids in the prevention of dental cavities.

Warnings

Keep out of reach of children under 6 years of age. If more than used for brushing is accidentally swallowed, get medical help or contact a Poison Control Center immediately.

Directions

do not swallow.

supervise children as necessary until capable of using without supervision.

Instruct children under 12 years of age in good brushing and rinsing habits (to minimize swallowing).

Adults and children 6 years of age and older: Brush teeth thoroughly, preferably after each meal or at least twice a day, or as directed by a dentist or a doctor.

Children under 2 years of age: Consult a dentist or doctor.

Inactive Ingredients

Liquid Sorbitol, Dental-Type Silica, Sodium Chloride, Sodium Lauryl sulphate, Sodium carboxymethylcellulose, Panthenol, Polyethylene Glycol 1500, Saccharin Sodium Hydrate, Phosphoric acid, Water

Dental Clinic 2080 Gingivalis Project K

Gingivitis-causing Bacteria

99% Inhibits

in-vitro test Results

Tested by Dental School Clinic

Dental Clinic 2080 K Toothpaste Citrus Cool Mint

OTC Drug

Customer Center:060-024-1357 (Nationwide Toll-Free)

We accept returns in compliance with the Consumer Protection Act of Fair Trade Commission.

AEKYUNG

MADE IN KOREA

www.aekyung.co.kr

Net Weight: 100g